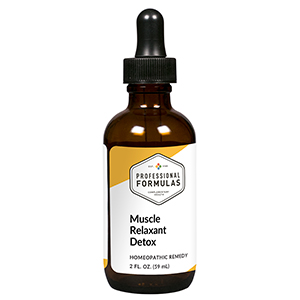 DRUG LABEL: Muscle Relaxant Detox
NDC: 63083-6051 | Form: LIQUID
Manufacturer: Professional Complementary Health Formulas
Category: homeopathic | Type: HUMAN OTC DRUG LABEL
Date: 20190815

ACTIVE INGREDIENTS: SUS SCROFA ADRENAL GLAND 6 [hp_X]/59 mL; BOS TAURUS BRAIN 6 [hp_X]/59 mL; BOS TAURUS HYPOTHALAMUS 6 [hp_X]/59 mL; BEEF LUNG 6 [hp_X]/59 mL; GELSEMIUM SEMPERVIRENS ROOT 15 [hp_X]/59 mL; CAPSICUM 15 [hp_X]/59 mL; AETHUSA CYNAPIUM WHOLE 30 [hp_X]/59 mL; ANTIMONY POTASSIUM TARTRATE 30 [hp_X]/59 mL; ANAMIRTA COCCULUS FRUIT 30 [hp_X]/59 mL; LYCOPODIUM CLAVATUM SPORE 30 [hp_X]/59 mL
INACTIVE INGREDIENTS: ALCOHOL; WATER

X51

ACTIVE INGREDIENTS

Adrenal 6X
Brain 6X
Hypothalamus 6X
Lung 6X
Gelsemium sempervirens 15X
Capsicum annuum 15X, 30X
Aethusa cynapium 30X
Antimonium tartaricum 30X
Cocculus indicus 30X
Lycopodium clavatum 30X
Mixed Isode 30C, 60C, 100C

QUESTIONS

Professional Formulas

PO Box 2034 Lake Oswego, OR 97035

INDICATIONS

For the temporary relief of skin flushing or redness, mild itching, nausea or vomiting, dizziness or lightheadedness, fatigue, or weakness due to sensitivity to or exposure to muscle relaxants.*

PURPOSE

*Claims based on traditional homeopathic practice, not accepted medical evidence. Not FDA evaluated.

WARNINGS

Consult a doctor if condition worsens or symptoms persist. Keep out of the reach of children. In case of overdose, get medical help or contact a poison control center right away. If pregnant or breastfeeding, ask a healthcare professional before use.

Keep out of the reach of children.

PREGNANCY OR BREAST FEEDING

If pregnant or breastfeeding, ask a healthcare professional before use.

DIRECTIONS

Place drops under tongue 30 minutes before/after meals. Adults and children 12 years and over: Take 10 drops up to 3 times per day. Consult a physician for use in children under 12 years of age.

OTHER INFORMATION

Tamper resistant. If seal is broken, do not use. After opening, close container tightly and store at room temperature away from heat.

INACTIVE INGREDIENTS

20% ethanol, purified water.

LABEL

Est 1985

Professional Formulas

Complementary Health

Muscle Relaxant Detox

Homeopathic Remedy

2 FL. OZ. (59 mL)